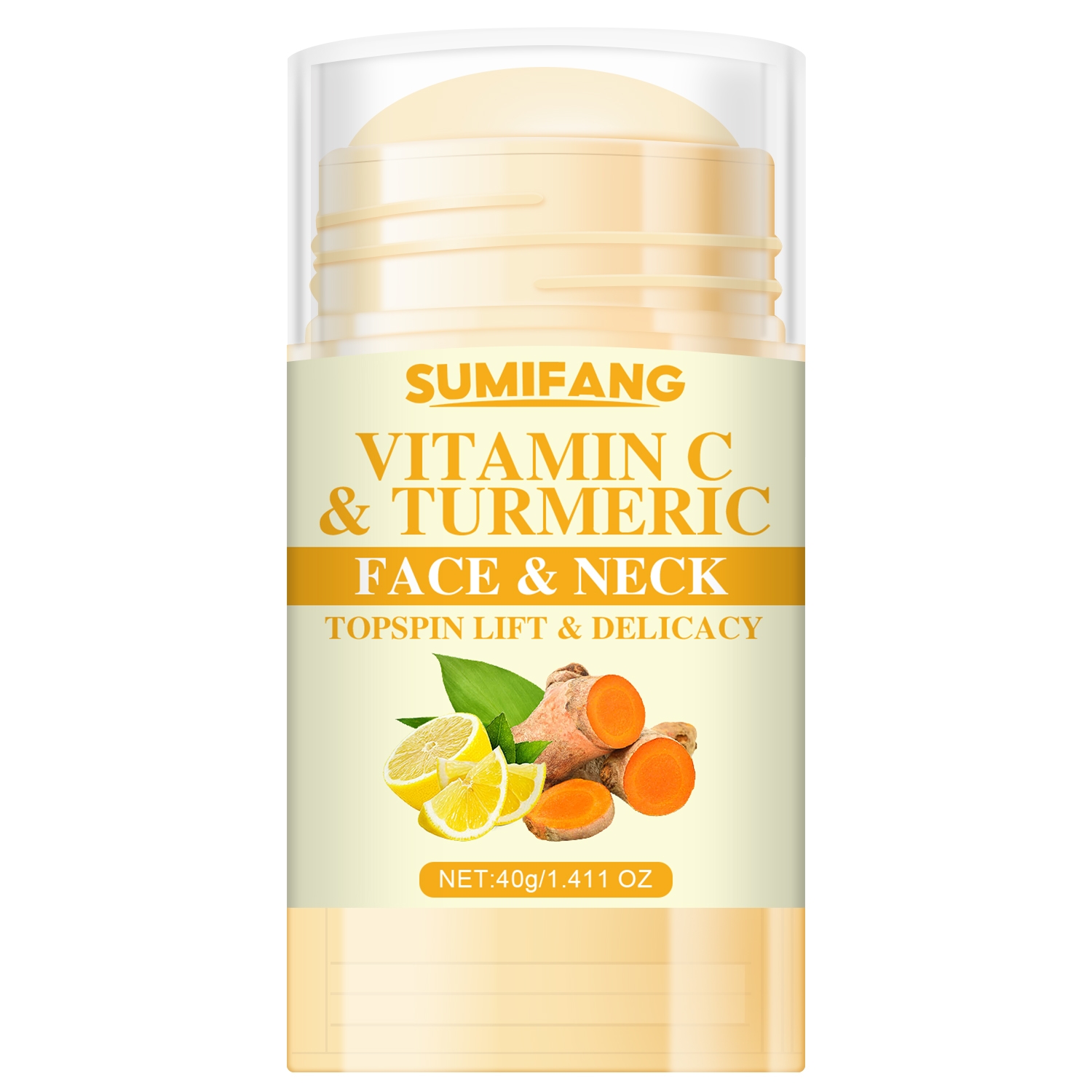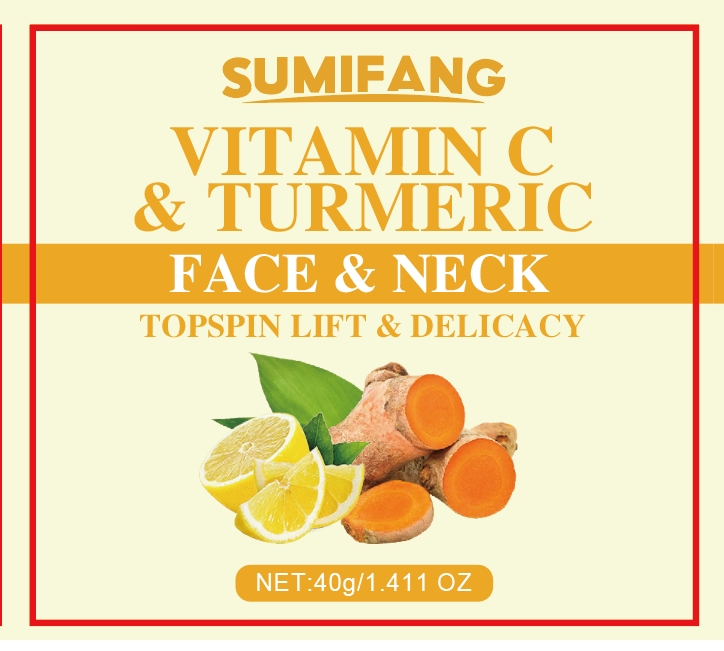 DRUG LABEL: VITAMIN C TURMERIC FACENECK
NDC: 84025-108 | Form: STICK
Manufacturer: Guangzhou Yanxi Biotechnology Co.. Ltd
Category: otc | Type: HUMAN OTC DRUG LABEL
Date: 20240801

ACTIVE INGREDIENTS: MINERAL OIL 5 mg/40 g; HYDROGENATED AVOCADO OIL 3 mg/40 g
INACTIVE INGREDIENTS: WATER

DOSAGE AND ADMINISTRATION

Moisturizing Care Screw Stick for Neck Skin

WARNINGS

Keep out of children

INACTIVE INGREDIENT

Aqua

INDICATIONS AND USAGE

For daily skin care

keep out of children

PURPOSE

Moisturizes and smoothes skin